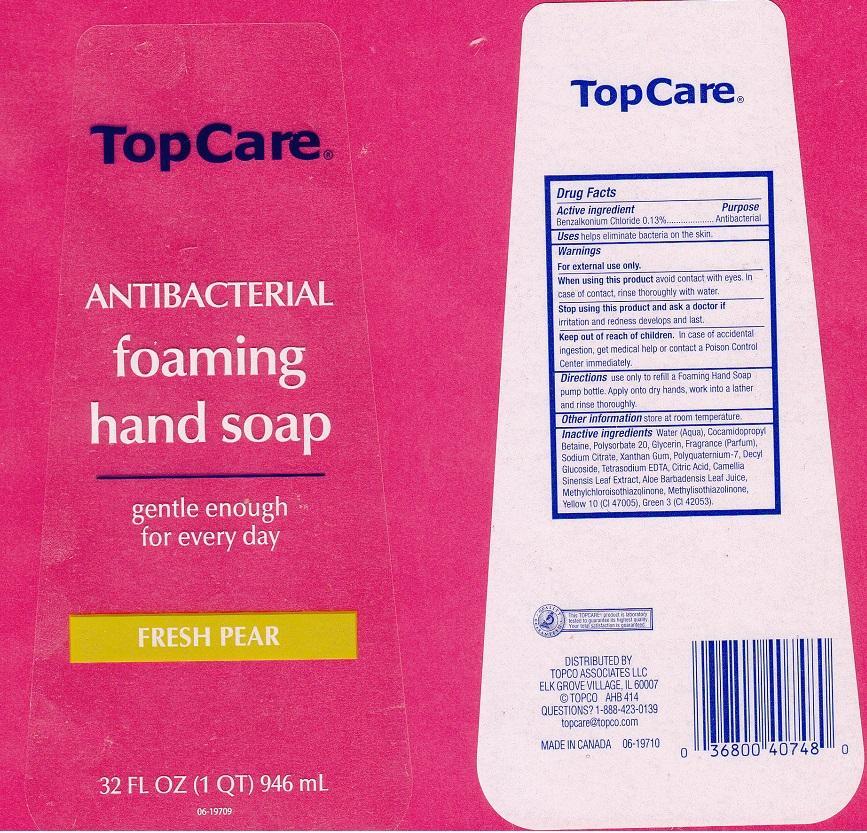 DRUG LABEL: TOPCARE
NDC: 36800-109 | Form: LIQUID
Manufacturer: TOPCO ASSOCIATES LLC
Category: otc | Type: HUMAN OTC DRUG LABEL
Date: 20140729

ACTIVE INGREDIENTS: BENZALKONIUM CHLORIDE 1.3 mg/1 mL
INACTIVE INGREDIENTS: WATER; COCAMIDOPROPYL BETAINE; POLYSORBATE 20; GLYCERIN; SODIUM CITRATE; XANTHAN GUM; POLYQUATERNIUM-7 (70/30 ACRYLAMIDE/DADMAC; 1600000 MW); DECYL GLUCOSIDE; EDETATE SODIUM; CITRIC ACID MONOHYDRATE; GREEN TEA LEAF; ALOE VERA LEAF; METHYLCHLOROISOTHIAZOLINONE; METHYLISOTHIAZOLINONE; D&C YELLOW NO. 10; FD&C GREEN NO. 3

DRUG FACTS

ACTIVE INGREDIENT

BENZALKONIUM CHLORIDE 0.13%

PURPOSE

ANTIBACTERIAL

USES

HELPS ELIMINATE BACTERIA ON THE SKIN

WARNINGS

FOR EXTERNAL USE ONLY

WHEN USING THIS PRODUCT

AVOID CONTACT WITH EYES. IN CASE OF CONTACT, RINSE THOROUGHLY WITH WATER

STOP USING THIS PRODUCT AND ASK A DOCTOR IF

IRRITATION AND REDNESS DEVELOPS AND LASTS

KEEP OUT OF REACH OF CHILDREN

IN CASE OF ACCIDENTAL INGESTION, GET MEDICAL HELP OR CONTACT A POISON CONTROL CENTER IMMEDIATELY

DIRECTIONS

USE ONLY TO REFILL A FOAMING HAND SOAP PUMP BOTTLE. APPLY ONTO DRY HANDS, WORK INTO A LATHER AND RINSE THOROUGHLY

OTHER INFORMATION

STORE AT ROOM TEMPERATURE

INACTIVE INGREDIENTS

WATER (AQUA), COCAMIDOPROPYL BETAINE, POLYSORBATE 20, GLYCERIN, FRAGRANCE (PARFUM), SODIUM CITRATE, XANTHAN GUM, POLYQUATERNIUM-7, DECYL GLUCOSIDE, TETRASODIUM EDTA, CITRIC ACID, CAMELLIA SINENSIS LEAF EXTRACT, ALOE BARBADENSIS LEAF JUICE, METHYLCHLOROISOTHIAZOLINONE, METHYLISOTHIAZOLINOEN, YELLOW 10 (CI 47005), GREEN 3 (CI 42053)